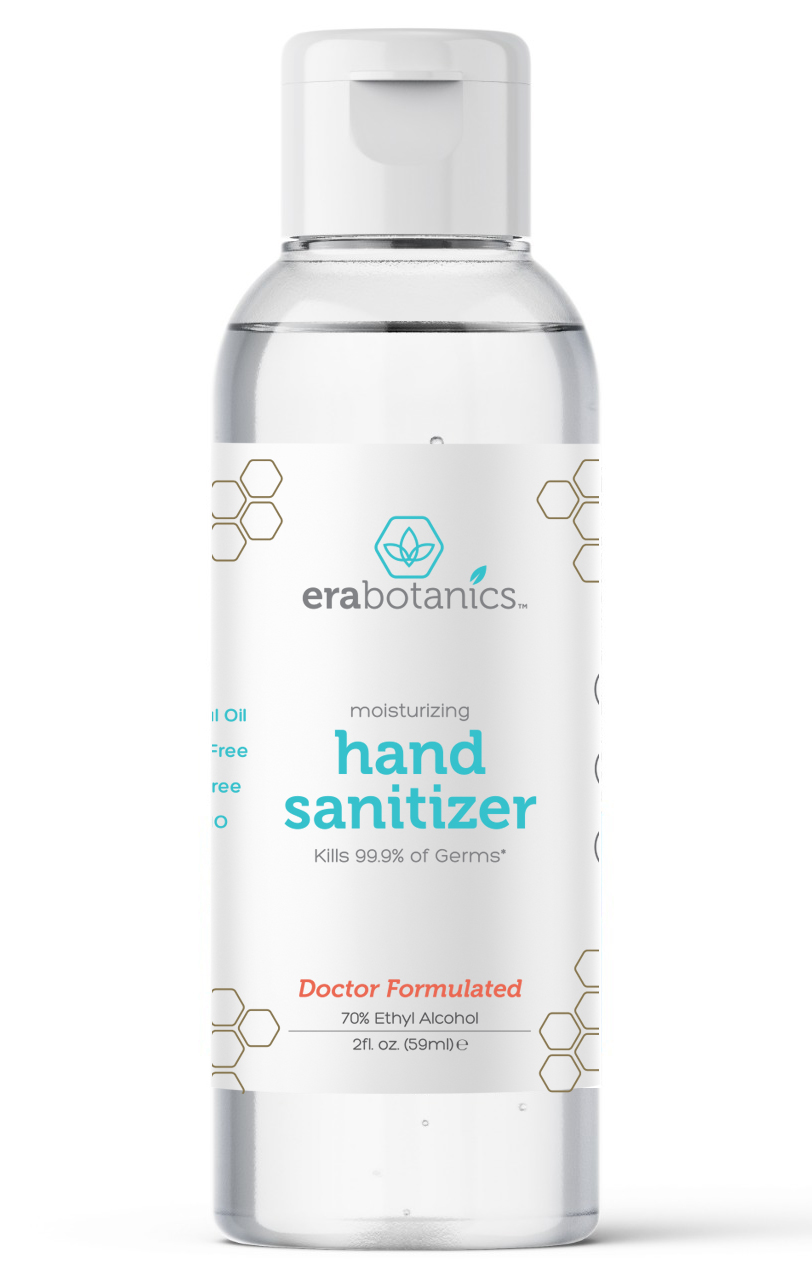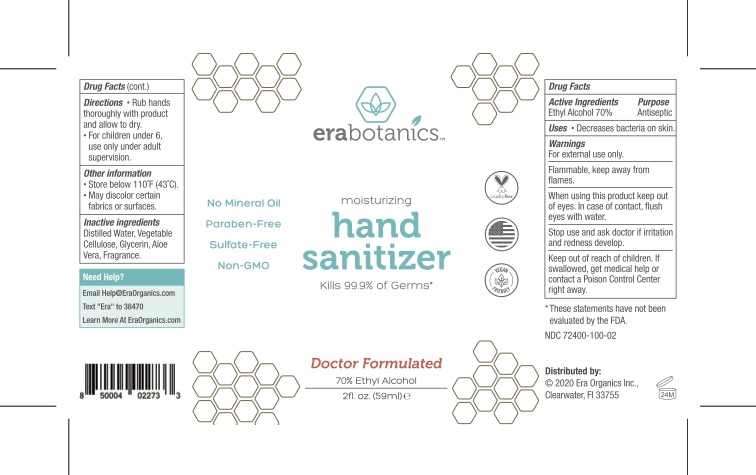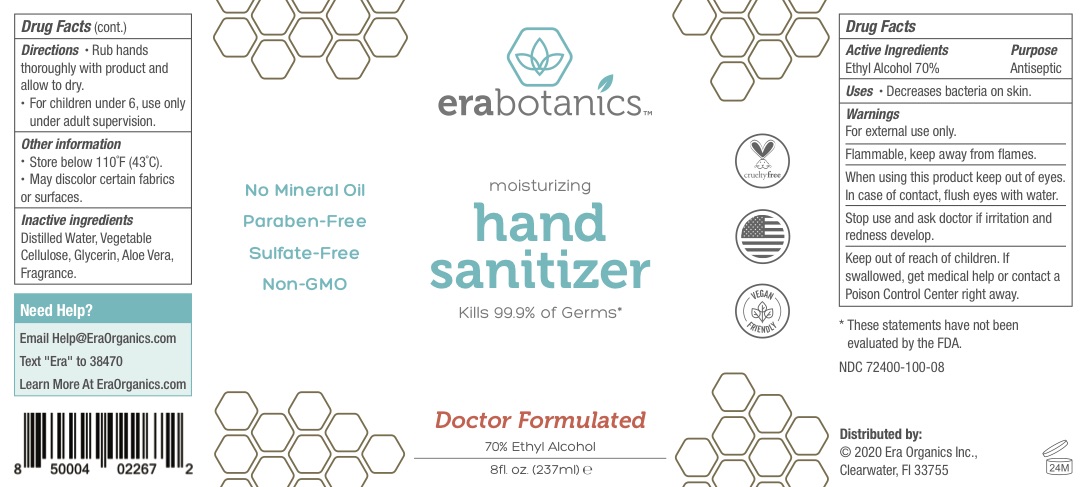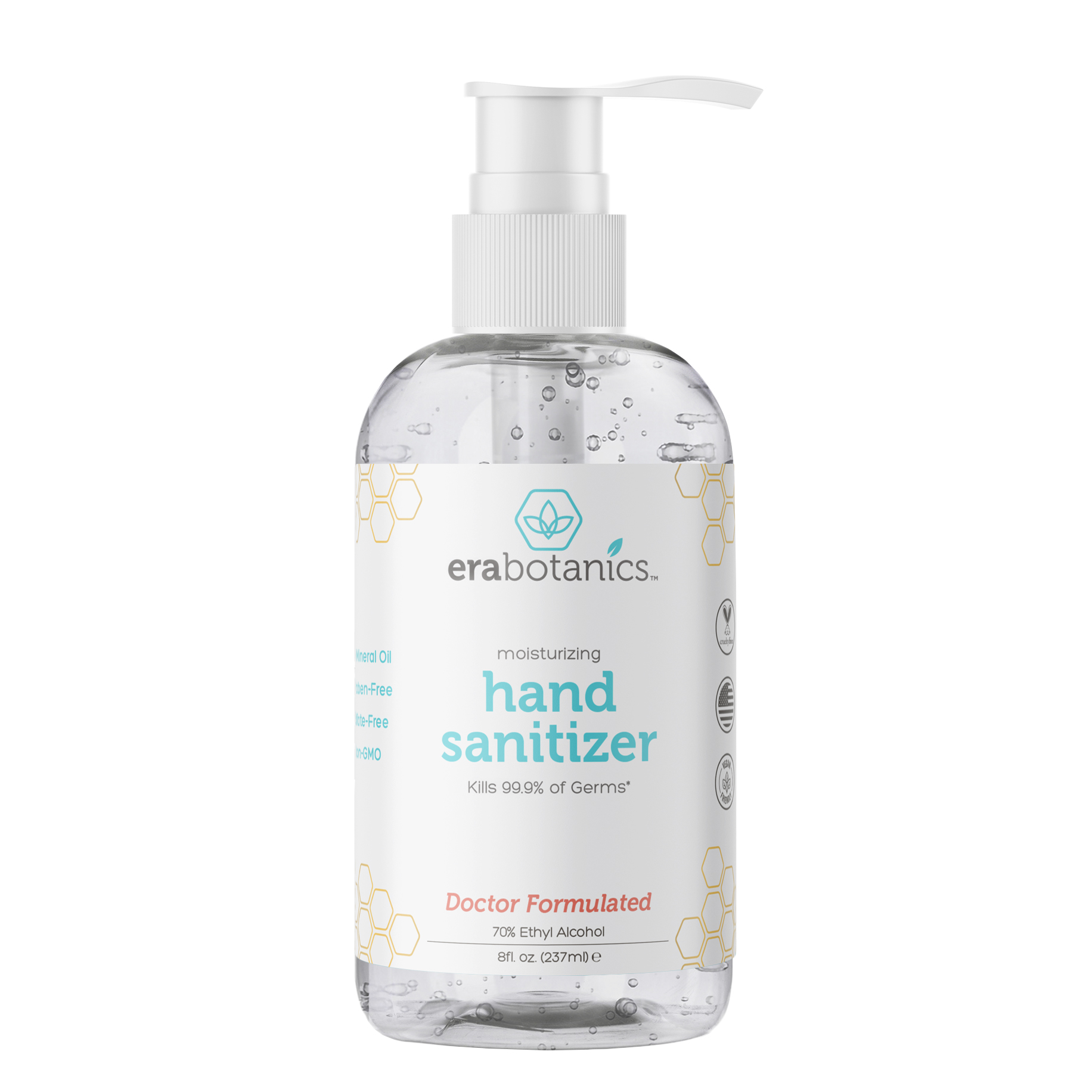 DRUG LABEL: LifeShield Hand Sanitizer 70% EtOH
NDC: 72400-100 | Form: GEL
Manufacturer: Era Organics
Category: otc | Type: HUMAN OTC DRUG LABEL
Date: 20200623

ACTIVE INGREDIENTS: ALCOHOL 70.7 mL/100 mL
INACTIVE INGREDIENTS: WATER 28.5 mL/100 mL; LIMONENE, (+)- 0.1 mL/100 mL; HYDROXYPROPYL CELLULOSE, UNSPECIFIED 0.01 mL/100 mL; GLYCERIN 0.7 mL/100 mL; ALOE VERA LEAF POLYSACCHARIDES 0.01 mL/100 mL

Hand Sanitizer Gel

Active Ingredients

Ethyl Alcohol 70%

Purpose

Antiseptic

Uses

Decreases bacteria on skin.

Warnings

For external use only.

Flammable, keep away from flames.

When using this product keep out of eyes. In case of contact, flush eyes with water.

Stop use and ask doctor if irritation and redness develop.

Keep out of reach of children. If swallowed, get medical help or contact a Poison Control Center right away.

Directions

• Rub hands thoroughly with product and allow to dry.
• For children under 6, use only

under adult supervision.

Other information

• Store below 110 ̊F (43 ̊C).
• May discolor certain fabrics or surfaces.

Inactive ingredients

Distilled Water, Vegetable Cellulose, Glycerin, Aloe Vera, Fragrance.

Need Help?

Email Help@EraOrganics.com

Text "Era" to 38470
Learn More At EraOrganics.com